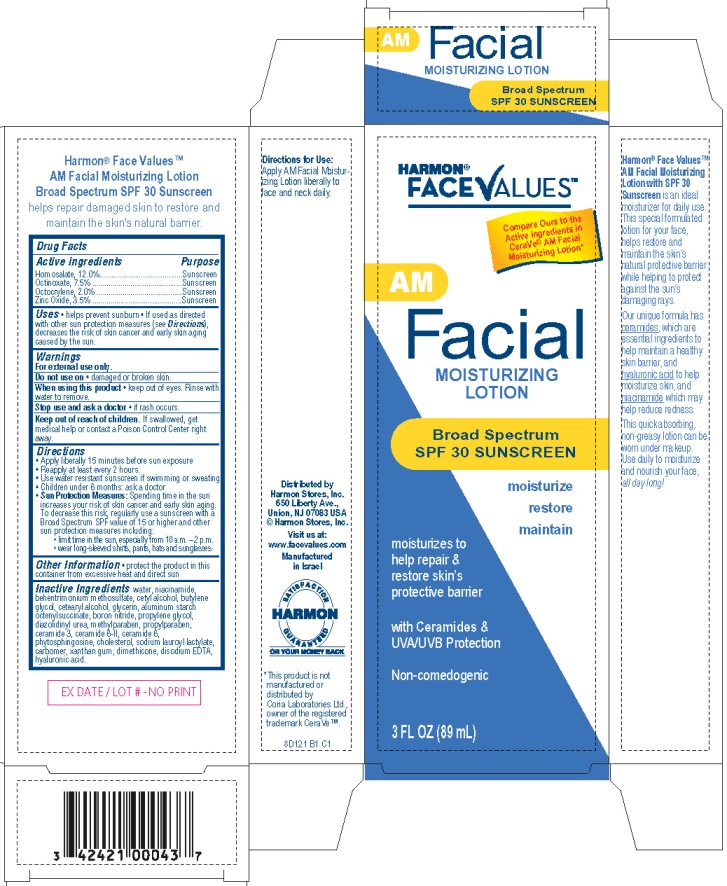 DRUG LABEL: Face Values - AM Facial Moisturizing Broad Spectrum SPF30 Sunscreen
NDC: 63940-121 | Form: LOTION
Manufacturer: Harmon Stores Inc
Category: otc | Type: HUMAN OTC DRUG LABEL
Date: 20131112

ACTIVE INGREDIENTS: HOMOSALATE 12 g/100 mL; OCTINOXATE 7.5 g/100 mL; OCTOCRYLENE 2 g/100 mL; ZINC OXIDE 3.5 g/100 mL
INACTIVE INGREDIENTS: WATER; NIACINAMIDE; BEHENTRIMONIUM METHOSULFATE; CETYL ALCOHOL; BUTYLENE GLYCOL; CETOSTEARYL ALCOHOL; GLYCERIN; ALUMINUM STARCH OCTENYLSUCCINATE; BORON NITRIDE; PROPYLENE GLYCOL; DIAZOLIDINYL UREA; METHYLPARABEN; PROPYLPARABEN; CERAMIDE 3; CERAMIDE 6 II; CERAMIDE 1; PHYTOSPHINGOSINE; CHOLESTEROL; SODIUM LAUROYL LACTYLATE; CARBOMER COPOLYMER TYPE A (ALLYL PENTAERYTHRITOL CROSSLINKED); XANTHAN GUM; DIMETHICONE; EDETATE DISODIUM; HYALURONIC ACID

Harmon® FaceValues™ AM Facial Moisturizing Lotion

Active ingredient

Homosalate 12.0%
Octinoxate 7.5%
Octocrylene 2.0%
Zinc Oxide 3.5%

Purpose

Sunscreen

Uses

- helps prevent sunburn
- If used as directed with other sun protection measures (see Directions), decreases the risk of skin cancer and early skin aging caused by the sun

Warnings

For external use only.

Do not use on

- damaged or broken skin.

When using this product

- keep out of eyes. Rinse with water to remove.

Stop use and ask a doctor

- if rash occurs.

Keep Out of Reach of Children.

If swallowed, get medical help or contact a Poison Control Center right away.

Directions

- Apply liberally 15 minutes before sun exposure.
- Reapply at least every 2 hours
- Use water resistant sunscreen if swimming or sweating
- Children under 6 months of age: ask a doctor
- Sun Protection Measures: Spending time in the sun increases your risk of skin cancer and early skin aging. To decrease this risk, regularly use a sunscreen with a Broad Spectrum SPF value of 15 or higher and other sun protection measures including:
  - limit time in the sun, especially from 10 a.m. - 2 p.m.
  - wear long-sleeved shirts, pants, hats and sunglasses

Other Information

- protect the product in this container from excessive heat and direct sun

Inactive ingredients

water, niacinamide, behentrimonium methosulfate, cetyl alcohol, butylene glycol, cetearyl alcohol, glycerin, aluminum starch octenylsuccinate, boron nitride, propylene glycol, diazolidinyl urea, methylparaben, propylparaben, ceramide 3, ceramide 6- II, ceramide 1, phytosphingosine, cholesterol, sodium lauroyl lactylate, carbomer, xanthan gum, dimethicone, disodium EDTA, hyaluronic acid

Package/Label Principal Display Panel

Harmon® FaceValuesTM AM Facial Moisturizing Lotion
Broad Spectrum SPF30 Sunscreen
moisturize
restore
maintain

moisturizes to help repair & restore skin's protective barrier

with Ceramides & UVA/UVB Protection

Non-comedogenic

Compare Ours to the Active ingredients in CeraVe®
AM Facial Moisturizing Lotion*

3 Fl Oz (89 mL)

Distributed by
Harmon Stores, Inc.
650 Liberty Ave.
Union, NJ 07083 USA
©Harmon Stores, Inc.
Visit us at:
www.facevalues.com

Manufactured in Israel

8D121 B1 C1

*This product is not manufactured or distributed by Coria Laboratories Ltd,
owner of the registered trademark CeraVeTM.

Label